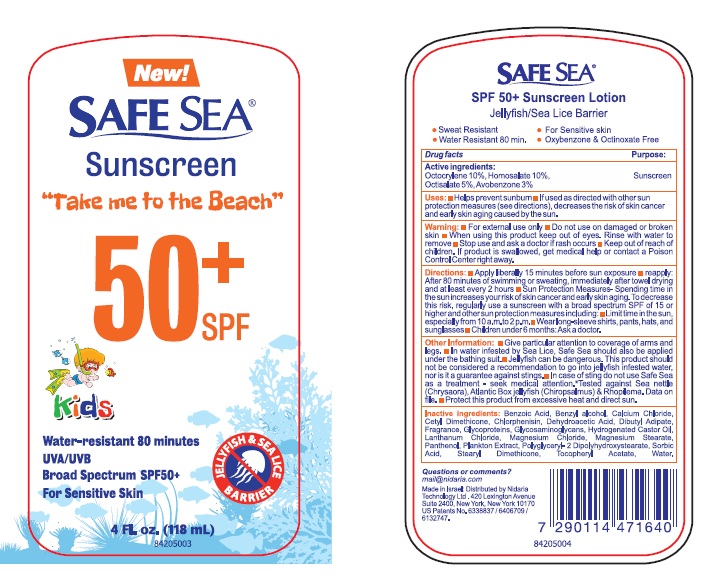 DRUG LABEL: Safe Sea SPF 50 kids
NDC: 65435-0200 | Form: LOTION
Manufacturer: NIDARIA TECHNOLOGY LTD
Category: otc | Type: HUMAN OTC DRUG LABEL
Date: 20251209

ACTIVE INGREDIENTS: OCTOCRYLENE 100 mg/1 mL; HOMOSALATE 100 mg/1 mL; OCTISALATE 50 mg/1 mL; AVOBENZONE 30 mg/1 mL
INACTIVE INGREDIENTS: WATER; DIBUTYL ADIPATE; POLYGLYCERYL-2 DIPOLYHYDROXYSTEARATE; STEARYL DIMETHICONE (400 MPA.S AT 50C); CETYL DIMETHICONE 25; PROPYLENE GLYCOL; HYDROGENATED CASTOR OIL; BENZYL ALCOHOL; LANTHANUM CHLORIDE; MAGNESIUM CHLORIDE; CALCIUM CHLORIDE; CHLORPHENESIN; PANTHENOL; .ALPHA.-TOCOPHEROL ACETATE; DEHYDROACETIC ACID; BENZOIC ACID; SORBIC ACID; PHAEODACTYLUM TRICORNUTUM; SACCHAROMYCES CEREVISIAE; POLYSULFATED GLYCOSAMINOGLYCAN

Safe Sea Sunscreen 50 SPF KIDS

: Active Ingredients

Octocrylene 10%

Homosalate 10%

Octisalate 5%

Avobenzone 3%

: Sunscreen Purpose

INDICATIONS AND USAGE

: ■ Helps prevent sunburn ■ If used as directed with other sun protection measures (see directions), decreases the risk of skin cancer and early skin aging caused by the sun. Uses

: ■ ■ Do not use on damaged or broken skin ■ When using this product keep out of eyes. Rinse with water to remove ■ Stop use and ask a doctor if rash occurs Warning For external use only

INSTRUCTIONS FOR USE

: ■ Apply liberally 15 minutes before sun exposure ■ reapply: After 80 minutes of swimming or sweating, immediately after towel drying and at least every 2 hours ■ Sun Protection Measures- Spending time in the sun increases your risk of skin cancer and early skin aging. To decrease this risk, regularly use a sunscreen with a broad spectrum SPF of 15 or higher and other sun protection measures including: ■ Limit time in the sun, especially from 10 a.m.to 2 p.m.■ Wear long-sleeve shirts, pants, hats, and sunglasses ■ Children under 6 months: Ask a doctor. Directions

KEEP OUT OF REACH OF CHILDREN

. If product is swallowed, get medical help or contact a Poison Control Center right away. Keep out of reach of children

OTHER SAFETY INFORMATION

: ■ Give particular attention to coverage of arms and legs. ■ In water infested by Sea Lice, Safe Sea should also be applied under the bathing suit.■ Jellyfish can be dangerous. This product should not be considered a recommendation to go into jellyfish infested water, nor is it a guarantee against stings.■ In case of sting do not use Safe Sea as a treatment - seek medical attention.*Tested against Sea nettle (Chrysaora), Atlantic Box jellyfish (Chiropsalmus) & Rhopilema. Data on file. ■ Protect this product from excessive heat and direct sun. Other Information

INACTIVE INGREDIENT

: Aqua, Dibutyl Adipate, Polyglyceryl 2 Dipolyhydroxystearate, Stearyl Dimethicone, Cetyl Dimethicone, Magnesium Stearate, Hydrogenated Castor Oil, Benzyl alcohol, Lanthanum Chloride, Magnesium Chloride, Calcium Chloride, Glycosaminoglycans, Glycoproteins, Plankton Extract, Parfum(Fragrance), Chlorphenisin, Panthenol, Tocopheryl Acetate, Dehydroacetic Acid, Benzoic Acid, Sorbic Acid Inactive Ingredients

Questions or comments?

mail@nidaria.com